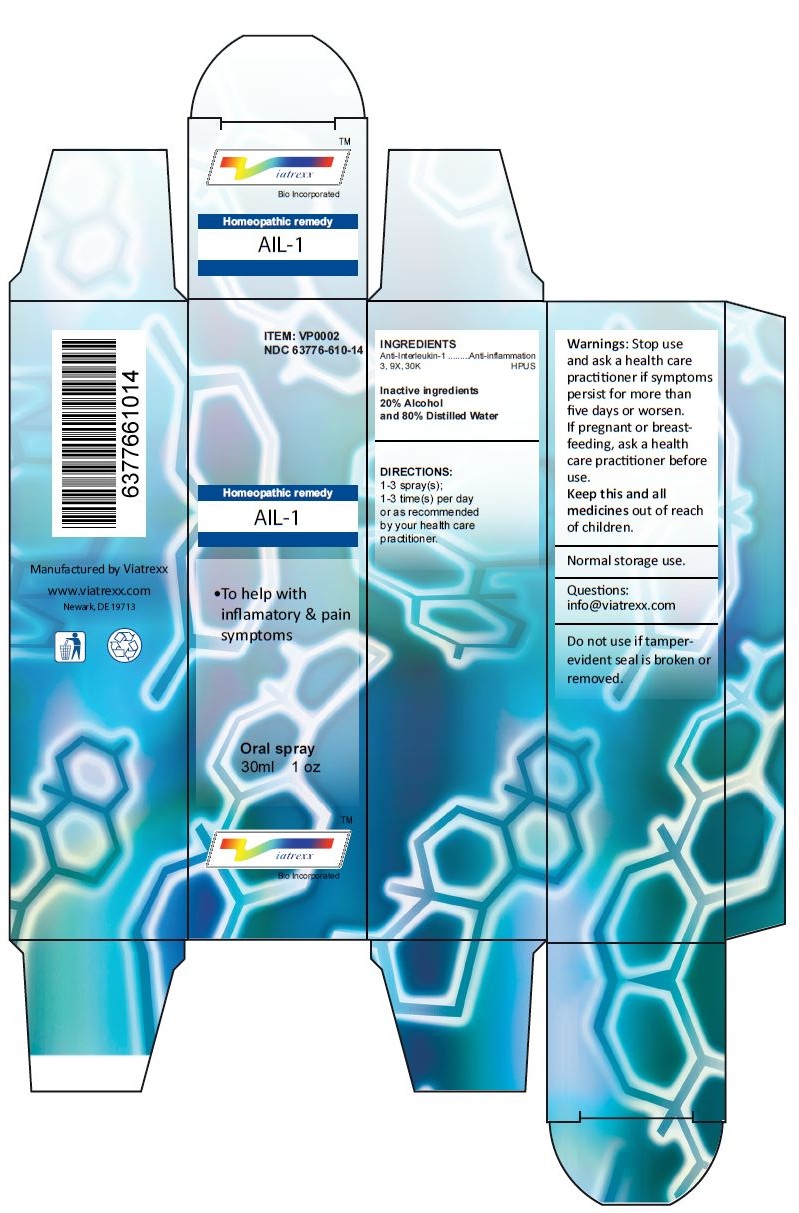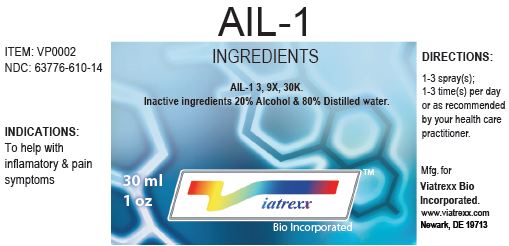 DRUG LABEL: AIL-1
NDC: 63776-610 | Form: SPRAY
Manufacturer: VIATREXX BIO INCORPORATED
Category: homeopathic | Type: HUMAN OTC DRUG LABEL
Date: 20221130

ACTIVE INGREDIENTS: ANTI-INTERLEUKIN-1.ALPHA. IMMUNOGLOBULIN G RABBIT 30 [kp_C]/1 mL
INACTIVE INGREDIENTS: ALCOHOL; WATER

AIL-1

Active Ingredients

Anti-Interleukin-1 3, 9X, 30K

Purpose:

Anti-Interleukin-1 | Anti-inflammation

Uses

To help with inflamatory & pain symptoms

Warnings

Stop use and ask a health care practitioner if symptoms persist for more than five days or worsen. If pregnant or breastfeeding, ask a health care practitioner before use.

Dosage

1-3 spray(s); 1-3 time(s) per day or as recommended by your health care practitioner.

KEEP OUT OF REACH OF CHILDREN

Keep this and all medicines out of reach of children.

Other Ingredients

20% Alcohol and 80% Water

Other Information

Normal storage use.
Do not use if tamper-evident seal is broken or removed.

Questions

info@viatrexx.com

Principal Display Panel

ITEM: VP0002
NDC 63776-610-14
Homeopathic remedy
AIL-1
• To help with inflamatory & pain symptoms
Oral spray
30ml 1 oz
Viatrexx™ Bio Incorporated
Manufactured by Viatrexx
www.viatrexx.com
Newark, DE 19713

AIL-1
30 ml
1 oz
Viatrexx™ Bio Incorporated
ITEM: VP0002
NDC: 63776-610-14
INDICATIONS:
To help with inflamatory & pain symptoms
DIRECTIONS:
1-3 spray(s); 1-3 time(s) per day or as recommended by your health care practitioner.
Mfg. for
Viatrexx Bio Incorporated.
www.viatrexx.com
Newark, DE 19713